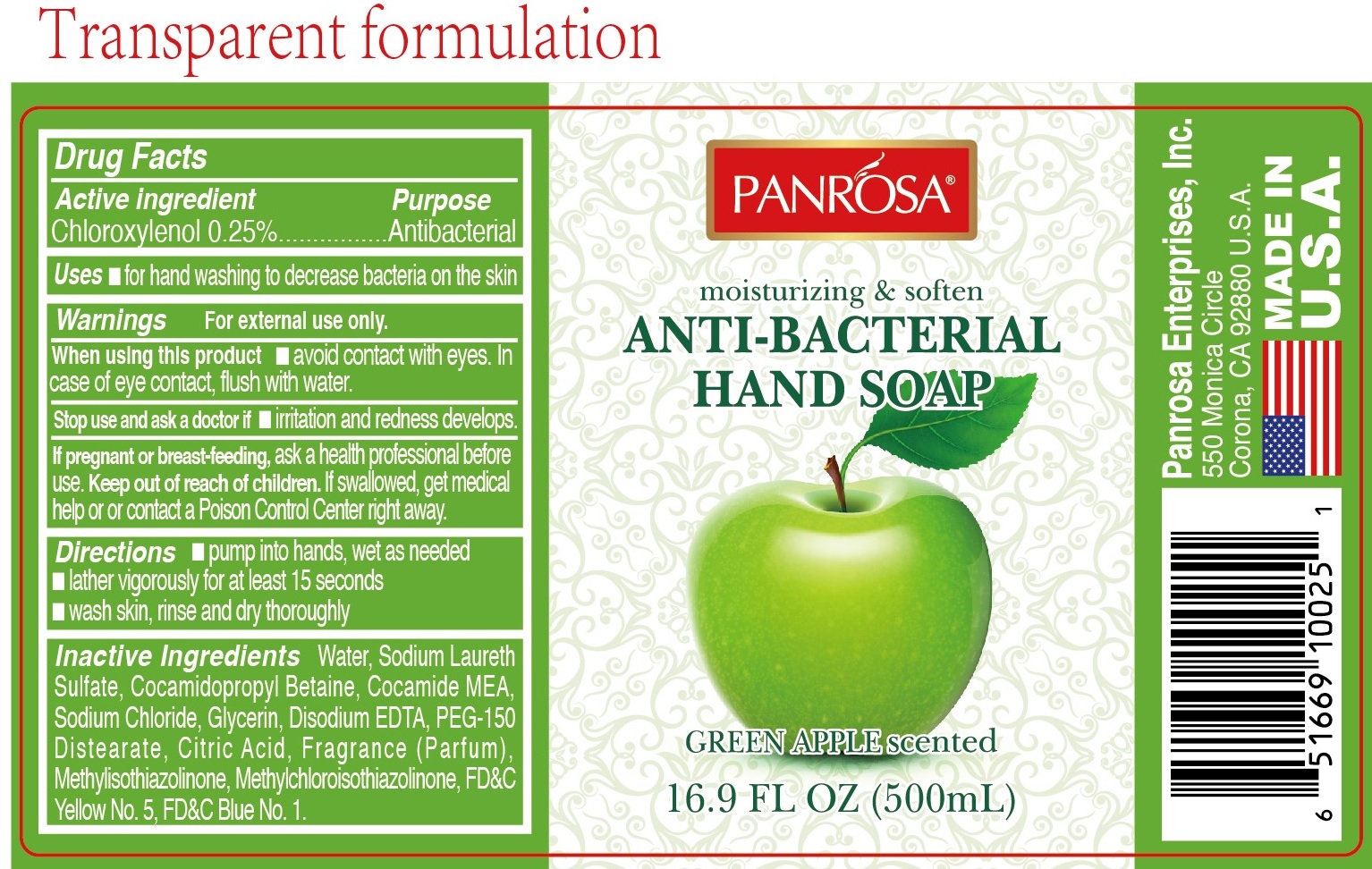 DRUG LABEL: Panrosa Antibacterial Hand Green Apple
NDC: 50302-015 | Form: GEL
Manufacturer: Panrosa Enterprises, Inc.
Category: otc | Type: HUMAN OTC DRUG LABEL
Date: 20200813

ACTIVE INGREDIENTS: CHLOROXYLENOL 2.5 mg/1 mL
INACTIVE INGREDIENTS: WATER; SODIUM LAURETH SULFATE; COCAMIDOPROPYL BETAINE; COCO MONOETHANOLAMIDE; SODIUM CHLORIDE; GLYCERIN; EDETATE DISODIUM ANHYDROUS; PEG-150 DISTEARATE; CITRIC ACID MONOHYDRATE; METHYLISOTHIAZOLINONE; METHYLCHLOROISOTHIAZOLINONE; FD&C YELLOW NO. 5; FD&C BLUE NO. 1

Panrosa Antibacterial Hand Soap - Green Apple

Active ingredient

Chloroxylenol 0.25%

Purpose

Antibacterial

Uses

- for hand washing to decrease bacteria on the skin

Warnings

For external use only.

When using this product

- avoid contact with eyes. In case of eye contact, flush with water.

Stop use and ask a doctor if

- irritation and redness develops.

If pregnant or breast-feeding,

ask a health professional before use

Keep out of reach of children.

If swallowed, get medical help or contact a Poison Control Center right away.

Directions

- pump into hands, wet as needed
- lather vigorously for at least 15 seconds
- wash skin, rinse and dry thoroughly

Inactive ingredients

Water, Sodium Laureth Sulfate, Cocamidopropyl Betaine, Cocamide MEA, Sodium Chloride, Glycerin, Disodium EDTA, PEG-150 Distearate, Citric Acid, Fragrance (Parfum), Methylisothiazolinone, Methylchloroisothiazolinone, FD&C Yellow No.5, FD&C Blue No.1.